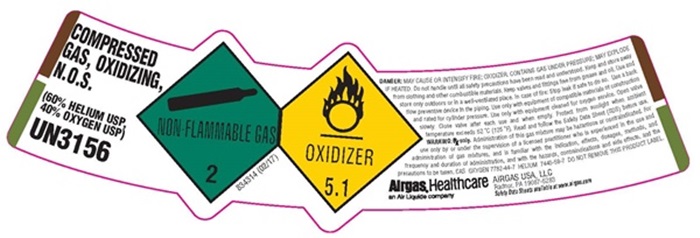 DRUG LABEL: Helium, Oxygen
NDC: 11054-042 | Form: GAS
Manufacturer: AIRGAS USA, LLC
Category: prescription | Type: HUMAN PRESCRIPTION DRUG LABEL
Date: 20241001

ACTIVE INGREDIENTS: HELIUM 600 mL/1 L; OXYGEN 400 mL/1 L

Helium Oxygen Mix 60/40

PACKAGE LABEL

OMPRESSED GAS, OXIDIZING, N.O.S.

(60% HELIUM USP, 40% OXYGEN USP)

UN3156

NON-FLAMMABLE GAS 2 834314 (02/17) OXIDIZER 5.1

DANGER: MAY CAUSE OR INTENSIFY FIRE: OXIDIZER CONTAINS GAS UNDER PRESSURE; MAY EXPLODE IF HEATED. Do not handle until all safety precautions have been read and understood. Use and store only outdoors or in a well-ventilated place. Use a back-flow preventative device in the piping. Use only with equipment of compatible materials of construction and rated for cylinder pressure. Close valve after each use and when empty. Protect from sunlight when ambient temperature exceeds 52oC/125oF. Read and follow the Safety Data Sheet (SDS) before use. WARNING: Rx only. Administration of this gas mixture may be hazardous or contraindicated. For use only by or under the supervision of a licensed practitioner who is experienced I the use and administration of gas mixtures, and is familiar with the indications, effects dosages, methods, and frequency and duration of administration and with the hazards, contraindications and side effects and the precautions to be taken. CAS OXYGEN 7782-44-7 HELIUM 7440-59-7 DO NOT REMOVE THIS PRODUCT LABEL

Airgas, Healthcare

An Air Liquide company

AIRGAS USA, LLC

Radnor, PA 19087-5283

Safety Data Sheets available at www. airgas.com